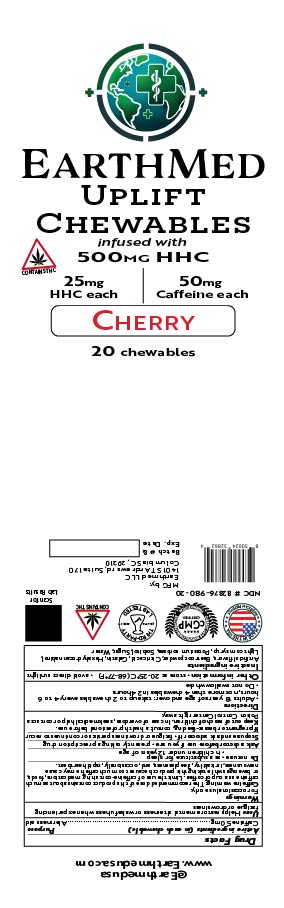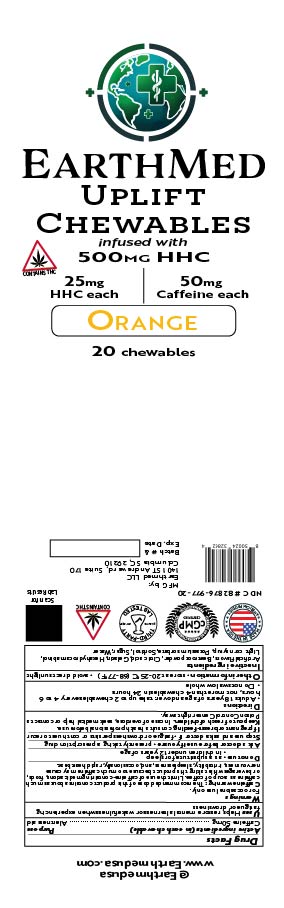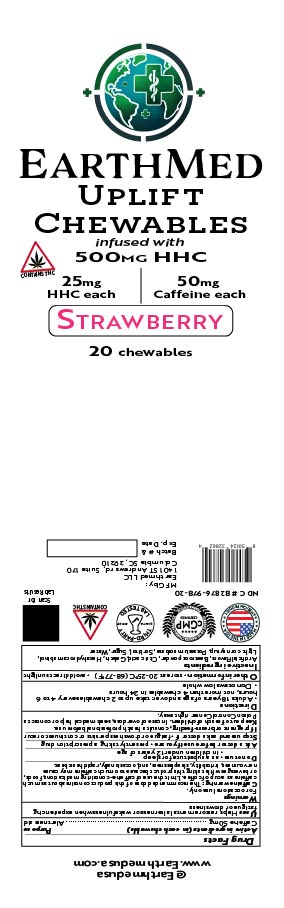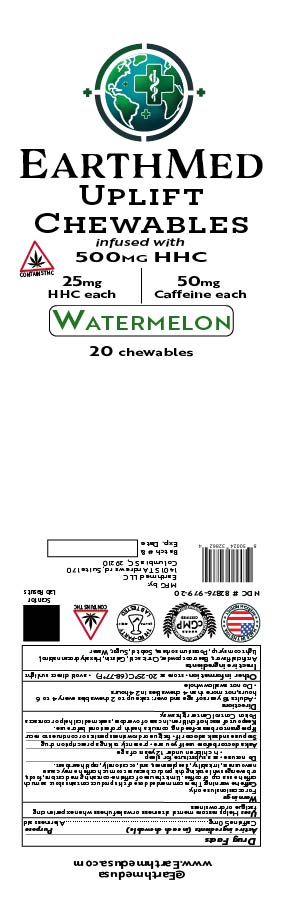 DRUG LABEL: Earthmed Uplift Chewable Orange
NDC: 82876-977 | Form: CHEWABLE GEL
Manufacturer: Earthmed LLC
Category: otc | Type: HUMAN OTC DRUG LABEL
Date: 20251114

ACTIVE INGREDIENTS: CAFFEINE 1 g/108.27 g
INACTIVE INGREDIENTS: SUCROSE 34.9 g/108.27 g; SORBITOL 2.9 g/108.27 g; GELATIN 6.78 g/108.27 g; HEXAHYDROCANNABINOL 0.575 g/108.27 g; ANHYDROUS CITRIC ACID 1.5 g/108.27 g; POTASSIUM SORBATE 0.1 g/108.27 g; BETA VULGARIS ROOT FRUCTOOLIGOSACCHARIDES 0.12 g/108.27 g; CORN SYRUP 34.9 g/108.27 g; WATER 26.75 g/108.27 g

Earthmed Uplift Chewables

Active ingredients (in each chewable)

Caffeine 50mg

Purpose

Alertness aid

Uses

Helps restore mental alertness or wakefulness when experiencing fatigue or drowsiness

Warnings

For occasional use only.

Caffeine warning. The recommended dose of this product contains about as much caffeine as a cup of coffee. limit the use of caffeine-containing medications, food, or beverages while taking this product because too much caffeine may cause nervousness, sleeplessness, and occasionally, rapid heartbeat.

Do not use

as a substitute for sleep, or in children under 12 years of age.

Ask a doctor before use if you are

Presently taking a prescription drug

Ask a doctor before use if you are

Presently taking a prescription drug

Stop using and ask a doctor if

fatigue or drowsiness persists or continues to recur

If pregnant or breast-feeding

consult a health professional before use

Keep out of reach of children

In case of overdose seek medical help or contact a poison control center right away

Keep out of reach of children

In case of overdose, seek medical help or contact a poison control center right away

Directions

Adults 18 years of age and over: take up to 2 chewables every 4 to 6 hours, not more that 4 chewable in 24 hours.

Do not swallow whole

Other information

Store at 68-77 degrees F

Avoid direct sunlight

Inactive ingredients

Artificial flavors, Citric acid, Gelatin, Hexahydrocannabinol, Light corn syrup, Potassium Sorbate, Sorbitol, Beet root powder, Sugar, Water.